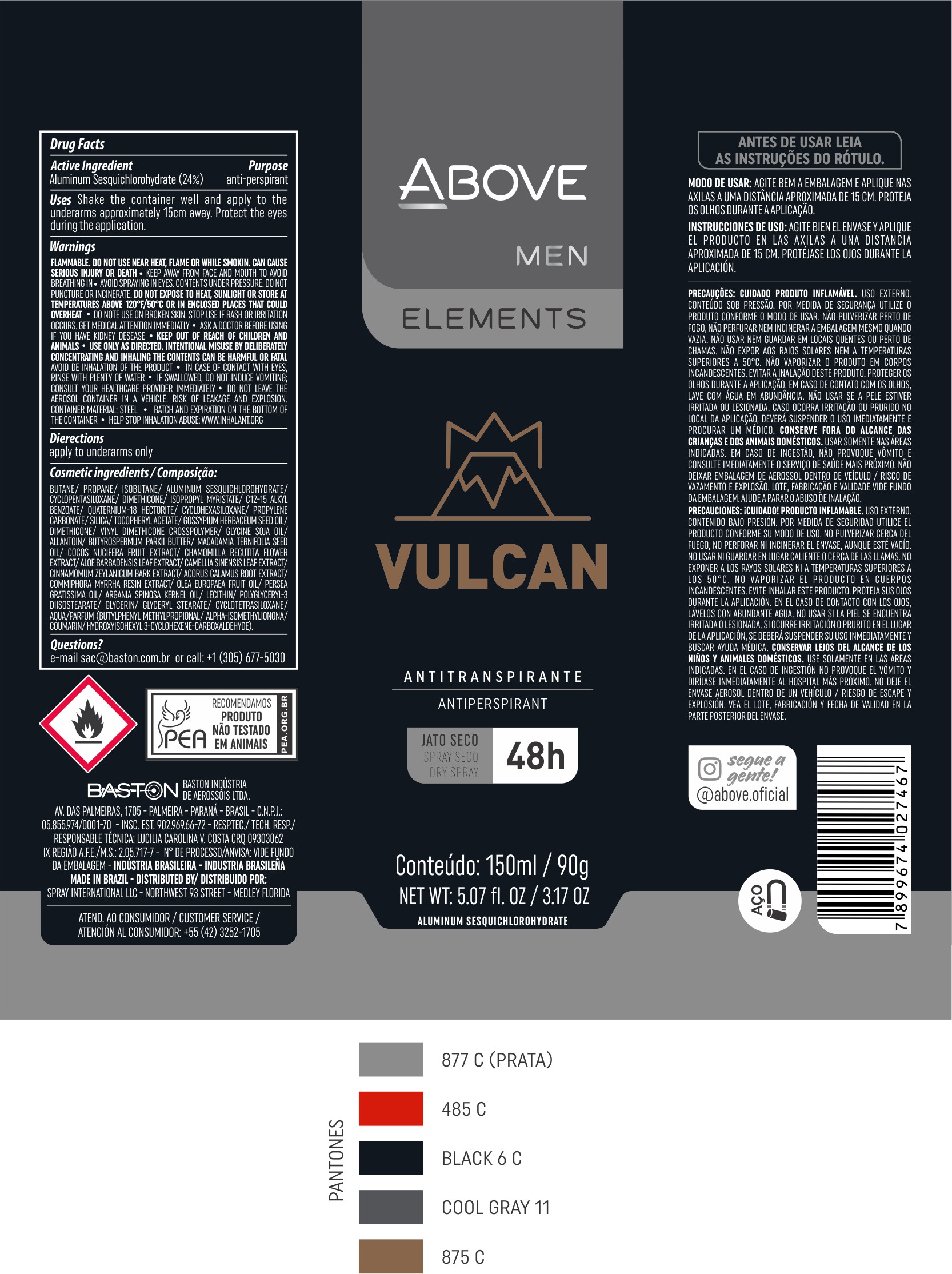 DRUG LABEL: Antiperspirant Above Elements Vulcan
NDC: 73306-1118 | Form: AEROSOL, SPRAY
Manufacturer: Baston Indústria de Aerossóis Ltda
Category: otc | Type: HUMAN OTC DRUG LABEL
Date: 20241226

ACTIVE INGREDIENTS: ALUMINUM SESQUICHLOROHYDRATE 24 g/100 g
INACTIVE INGREDIENTS: GLYCERYL MONOSTEARATE; WATER; AVOCADO OIL; CINNAMON BARK OIL; MACADAMIA OIL; SHEA BUTTER; PROPYLENE CARBONATE; ACORUS CALAMUS ROOT; DISTEARDIMONIUM HECTORITE; ISOPROPYL MYRISTATE; BUTANE; DIMETHICONE; SILICA DIMETHYL SILYLATE; COCONUT; CHAMOMILE; PROPANE; LECITHIN, SOYBEAN; ARGAN OIL; .ALPHA.-TOCOPHEROL ACETATE; ALLANTOIN; GLYCERIN; LEVANT COTTON SEED; POLYGLYCERYL-3 DIISOSTEARATE; ISOBUTANE; VINYL DIMETHICONE/METHICONE SILSESQUIOXANE CROSSPOLYMER; GREEN TEA LEAF; CYCLOMETHICONE 5; ALOE VERA LEAF; MYRRH OIL

Antiperspirant Above Elements Vulcan Aerosol